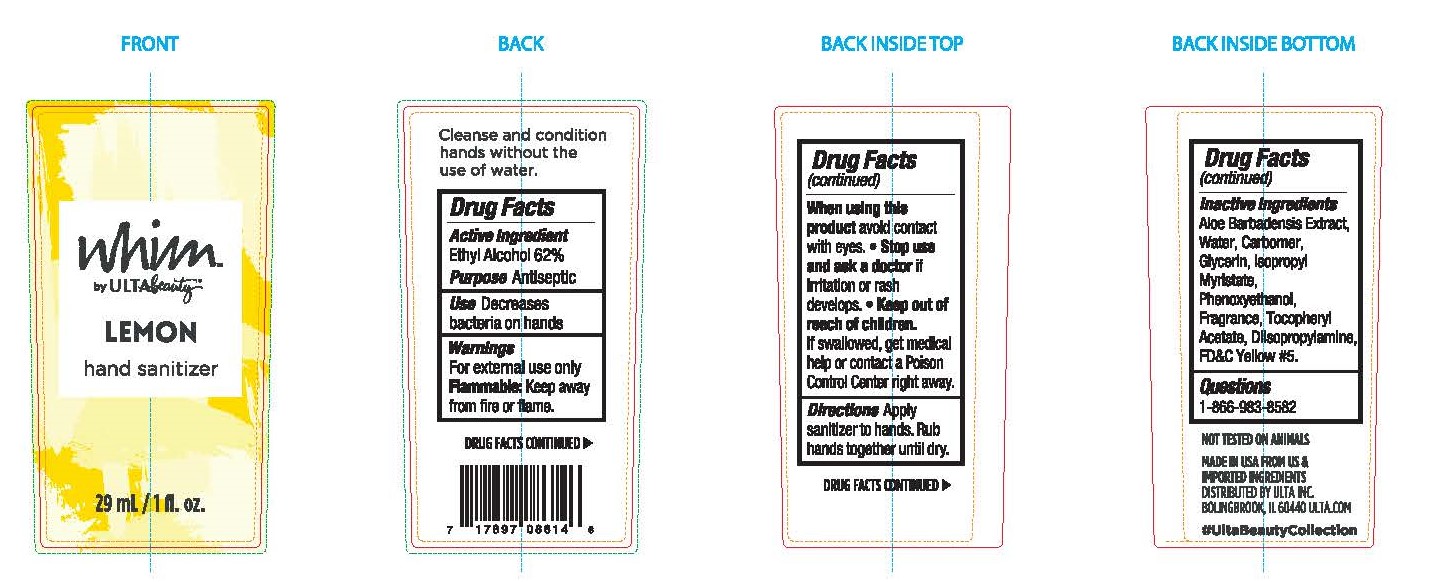 DRUG LABEL: ULTA WHIM
NDC: 73708-619 | Form: GEL
Manufacturer: Carrollclean
Category: otc | Type: HUMAN OTC DRUG LABEL
Date: 20200825

ACTIVE INGREDIENTS: ALCOHOL 62 mL/100 mL
INACTIVE INGREDIENTS: ISOPROPYL MYRISTATE 0.09 mL/100 mL; PHENOXYETHANOL 0.05 mL/100 mL; ALPHA-TOCOPHEROL ACETATE 0.01 mL/100 mL; DIISOPROPYLAMINE 0.21 mL/100 mL; WATER 31.5 mL/100 mL; ALOE VERA LEAF 0.9 mL/100 mL; GLYCERIN 0.19 mL/100 mL; CARBOMER INTERPOLYMER TYPE A (55000 CPS) 0.4 mL/100 mL

ULTA WHIM LEMON HAND SANITIZER

Use

Antiseptic

Active Ingredients

Ethyl Alcohol 62%

Use

Decreases bacteria on hands

Warnings

For external use only

FLAMMABLE: Keep away from fire or flame.

Inactive Ingredients

Aloe Barbadensis Extract, Water, Carbomer, Glycerin, Isopropyl Myristate, Phenoxyethanol, Fragrance, Tocopheryl Acetate, Diisopropylamine, FD&C Yellow #5

Dosage

Cleanse and condition hands without the use of water.

Keep Out of Reach of Children